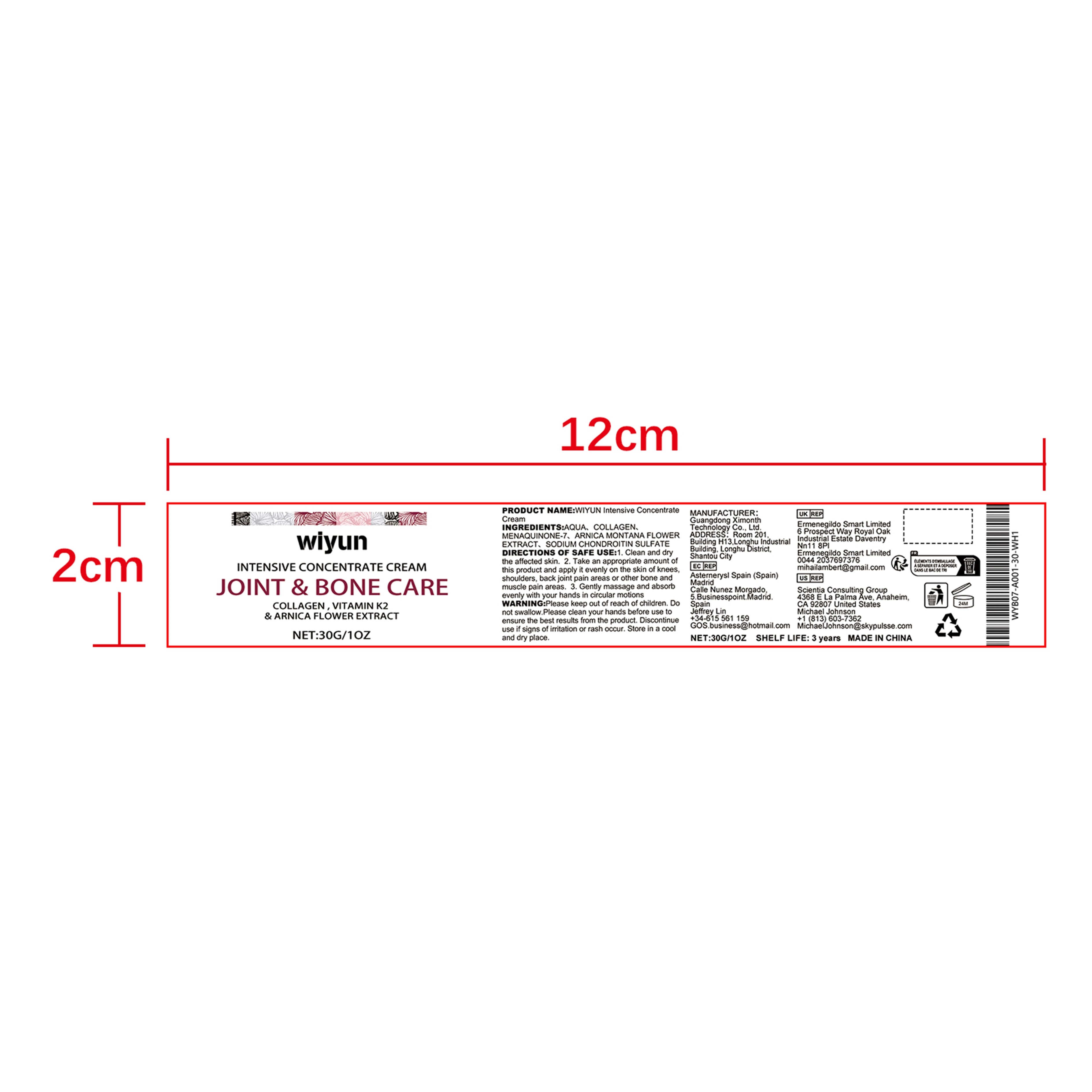 DRUG LABEL: JOINT BONE CARE
NDC: 84660-007 | Form: CREAM
Manufacturer: Guangdong Ximonth Technology Co., Ltd.
Category: otc | Type: HUMAN OTC DRUG LABEL
Date: 20240904

ACTIVE INGREDIENTS: MENAQUINONE 7 0.05 g/100 g; ARNICA MONTANA FLOWER 1 g/100 g; MARINE COLLAGEN, SOLUBLE 2 g/100 g
INACTIVE INGREDIENTS: SODIUM CHONDROITIN SULFATE (PORCINE; 5500 MW); WATER

Active Ingredient(s)

COLLAGEN 、MENAQUINONE-7 、ARNICA MONTANA FLOWER EXTRACT、SODIUM CHONDROITIN SULFATE

Purpose

Relieve joint&bone pain

Use

1. Clean and dry the affected skin. 2. Take an appropriate amount of this product and apply it evenly on the skin of knees, shoulders, back joint pain areas or other bone and muscle pain areas. 3. Gently massage and absorb evenly with your hands in circular motions.

Warnings

Please keep out of reach of children.Do not swallow.Please clean your hands before use to ensure the best results from the product.Discontinue use if signs of irritation or rash occur.Store in a cool and dry place.

Do not use

Discontinue use if signs of irritation or rash occur.

STOP USE

Discontinue use if signs of irritation or rash occur.

KEEP OUT OF REACH OF CHILDREN

Please keep out of reach of children. Do not swallow.

STORAGE AND HANDLING

Avoid freezing and excessive heat above 40C (104F) ）

Store in a cool and dry place.

INACTIVE INGREDIENT

AQUA